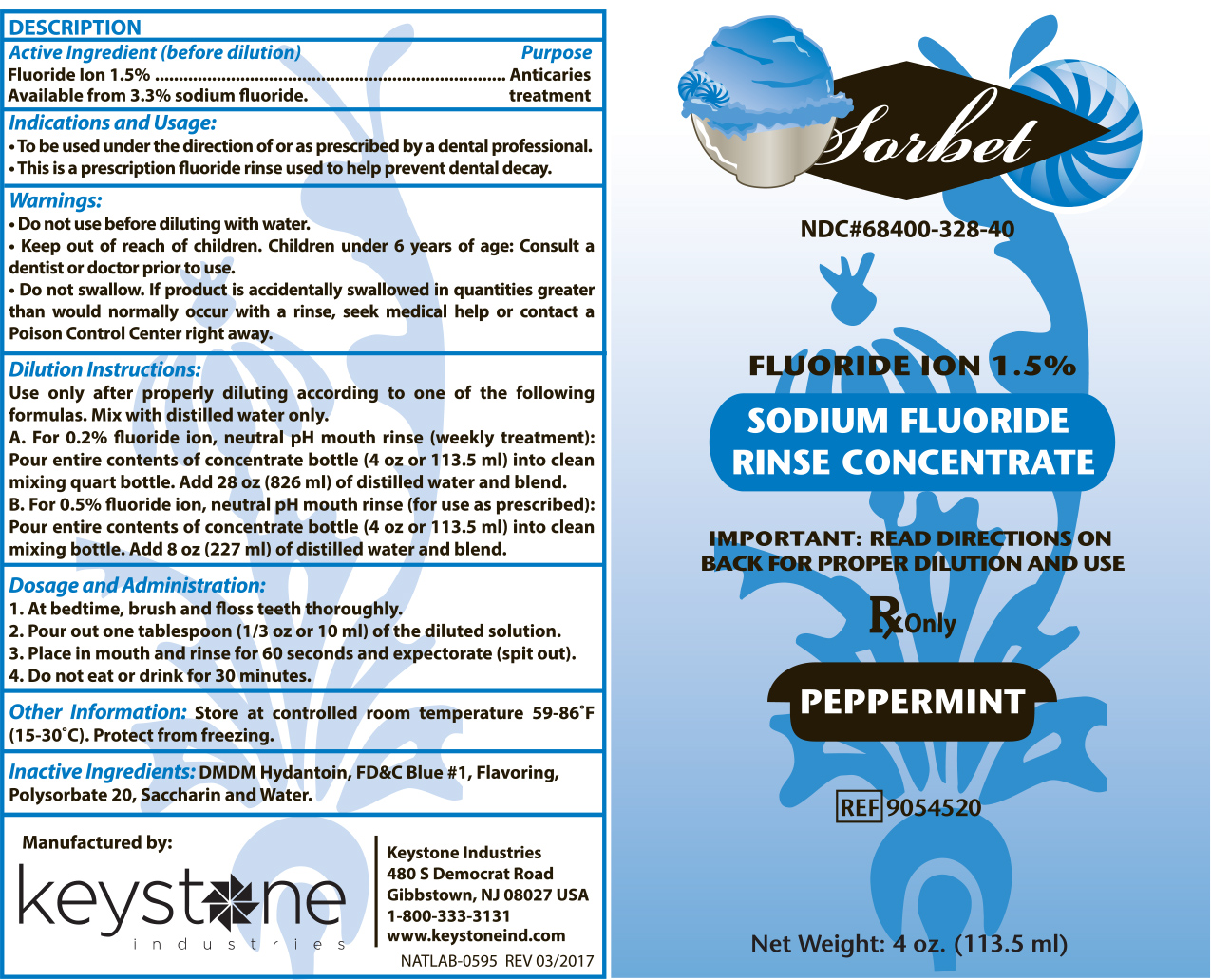 DRUG LABEL: Sorbet Rinse
NDC: 68400-328 | Form: CONCENTRATE
Manufacturer: Mycone Dental Supply Co., Inc DBA Keystone Industries and Deepak Products Inc
Category: prescription | Type: HUMAN PRESCRIPTION DRUG LABEL
Date: 20240424

ACTIVE INGREDIENTS: SODIUM FLUORIDE 1702.5 mg/113.5 mL
INACTIVE INGREDIENTS: DMDM HYDANTOIN; POLYSORBATE 20; SACCHARIN SODIUM; WATER; FD&C BLUE NO. 1

Active Ingredient (before dilution):

Fluoride Ion 1.5%

Available from 3.3% Sodium fluoride.

Purpose:

Anticaries Treatment

Indications and Usage:

- To be used under the direction of or as prescribed by a dental professional.
- This is a prescription fluoride rinse used to help prevent dental decay.

Warnings:

- Do not use before diluting with water.
- Keep out of reach of children. Children under 6 years of age: Consult a dentist or doctor prior to use.
- Do not swallow. If product is accidentally swallowed in quantities greater than would normally occur with a rinse, seek medical help or contact a Poison Control Center right away.

Dilution Instructions:

Use only after properly diluting according to one of the following formulas. Mix with distilled water only.

A. For 0.2% fluoride ion, neutral pH mouth rinse (weekly treatment):

Pour entire contents of concentrate bottle (4oz or 113.5mL) into clean mixing quart bottle. Add 28oz (286mL) of distilled water and blend.

B. For 0.5% fluoride ion, neutral pH mouth rinse (for use as prescribed):

Pour entire contents of concentrate bottle (4oz or 113.5mL) into clean mixing bottle. Add 8oz (227mL) of distilled water and blend.

Dosage and Administration:

1. At bedtime, brush and floss teeth thoroughly.

2. Pour out one tablespoon (1/3oz or 10mL) of the diluted solution.

3. Place in mouth and rinse for 60 seconds and expectorate (spit out).

4. Do not eat or drink for 30 minutes.

Other Information:

Store at controlled room temperature 59-86°F (15-30°C). Protect from freezing.

Inactive Ingredients:

DMDM Hydantoin, FD&C Blue #1, Flavoring, Polysorbate 20, Saccharin and Water.